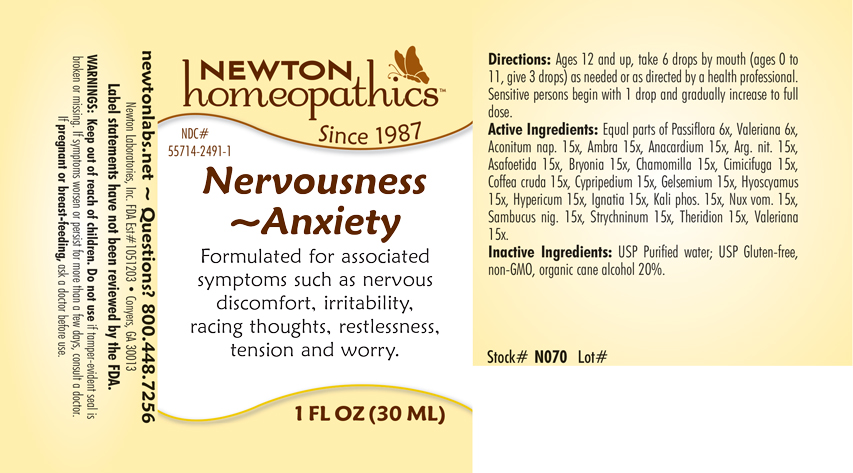 DRUG LABEL: Nervousness - Anxiety
NDC: 55714-2491 | Form: LIQUID
Manufacturer: Newton Laboratories, Inc.
Category: homeopathic | Type: HUMAN OTC DRUG LABEL
Date: 20250207

ACTIVE INGREDIENTS: ACONITUM NAPELLUS 15 [hp_X]/1 mL; AMBERGRIS 15 [hp_X]/1 mL; SEMECARPUS ANACARDIUM JUICE 15 [hp_X]/1 mL; SILVER NITRATE 15 [hp_X]/1 mL; FERULA ASSA-FOETIDA RESIN 15 [hp_X]/1 mL; BRYONIA ALBA ROOT 15 [hp_X]/1 mL; MATRICARIA CHAMOMILLA 15 [hp_X]/1 mL; BLACK COHOSH 15 [hp_X]/1 mL; ARABICA COFFEE BEAN 15 [hp_X]/1 mL; CYPRIPEDIUM PARVIFLORUM VAR. PUBESCENS ROOT 15 [hp_X]/1 mL; GELSEMIUM SEMPERVIRENS ROOT 15 [hp_X]/1 mL; HYOSCYAMUS NIGER 15 [hp_X]/1 mL; HYPERICUM PERFORATUM 15 [hp_X]/1 mL; STRYCHNOS IGNATII SEED 15 [hp_X]/1 mL; DIBASIC POTASSIUM PHOSPHATE 15 [hp_X]/1 mL; STRYCHNOS NUX-VOMICA SEED 15 [hp_X]/1 mL; SAMBUCUS NIGRA FLOWERING TOP 15 [hp_X]/1 mL; STRYCHNINE 15 [hp_X]/1 mL; THERIDION CURASSAVICUM 15 [hp_X]/1 mL; VALERIAN 15 [hp_X]/1 mL; PASSIFLORA INCARNATA FLOWERING TOP 6 [hp_X]/1 mL
INACTIVE INGREDIENTS: ALCOHOL; WATER

Nervousness 2491L

INDICATIONS & USAGE SECTION

Formulated for associated symptoms such as nervous discomfort, irritability, racing thoughts, restlessness, tension and worry.

DOSAGE & ADMINISTRATION SECTION

Directions: Ages 12 and up, take 6 drops by mouth (ages 0 to 11, give 3 drops) as needed or as directed by a health professional. Sensitive persons begin with 1 drop and gradually increase to full dose.

OTC - ACTIVE INGREDIENT SECTION

Equal parts of Passiflora incarnata 6x, Valeriana officinalis 6x, Aconitum napellus 15x, Ambra grisea 15x, Anacardium orientale 15x, Argentum nitricum 15x, Asafoetida 15x, Bryonia 15x, Chamomilla 15x, Cimicifuga racemosa 15x, Coffea cruda 15x, Cypripedium pubescens 15x, Gelsemium sempervirens 15x, Hyoscyamus niger 15x, Hypericum perforatum 15x, Ignatia amara 15x, Kali phosphoricum 15x, Nux vomica 15x, Sambucus nigra 15x, Strychninum 15x, Theridion 15x, Valeriana officinalis 15x.

OTC - PURPOSE SECTION

Formulated for associated symptoms such as nervous discomfort, irritability, racing thoughts, restlessness, tension and worry.

INACTIVE INGREDIENT SECTION

Inactive Ingredients: USP Purified Water; USP Gluten-free, non-GMO, organic cane alcohol 20%.

QUESTIONS SECTION

newtonlabs.net – Questions? 800.448.7256

Newton Laboratories, Inc. FDA Est # 1051203 - Conyers, GA 30013

WARNINGS SECTION

WARNINGS: Keep out of reach of children. Do not use if tamper-evident seal is broken or missing. If symptoms worsen or persist for more than a few days, consult a doctor. If pregnant or breast-feeding, ask a doctor before use.

OTC - PREGNANCY OR BREAST FEEDING SECTION

If pregnant or breast-feeding, ask a doctor before use.

OTC - KEEP OUT OF REACH OF CHILDREN SECTION

Keep out of reach of children.